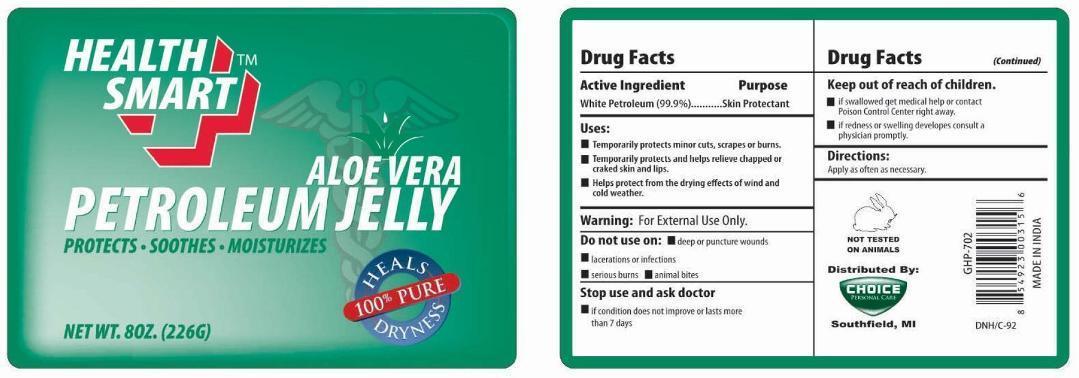 DRUG LABEL: Health Smart Aloe Vera Petroleum
NDC: 52862-012 | Form: JELLY
Manufacturer: Home Smart Products
Category: otc | Type: HUMAN OTC DRUG LABEL
Date: 20241219

ACTIVE INGREDIENTS: PETROLATUM 99.9 g/100 g
INACTIVE INGREDIENTS: WATER 0.1 g/100 g

Active Ingredient

White Petroleum (99.9%)

Purpose

Skin Protectant

Uses:

- Temporarily protects minor cuts, scrapes or burns.
- Temporarily protects and helps relieve chapped or cracked skin and lips.
- Helps protect from the drying effects of wind and cold weather.

Warning:

For External Use Only.

Do not use on:

- deep or puncture wounds
- lacerations or infections
- serious burns
- animal bites

Stop use and ask doctor

- if condition does not improve or lasts more than 7 days.

Keep out of reach of children

- if swallowed get medical help or contact Poison Control Center right away.
- if redness or swelling developes, consult a physician promptly.

Directions:

Apply as often as necessary.

Inactive Ingredients:

None.

PACKAGE LABEL

PRINCIPAL DISPLAY PANEL

HEALTH SMART ALOE VERA PETROLEUM JELLY

NET WT. 8OZ. (226G)